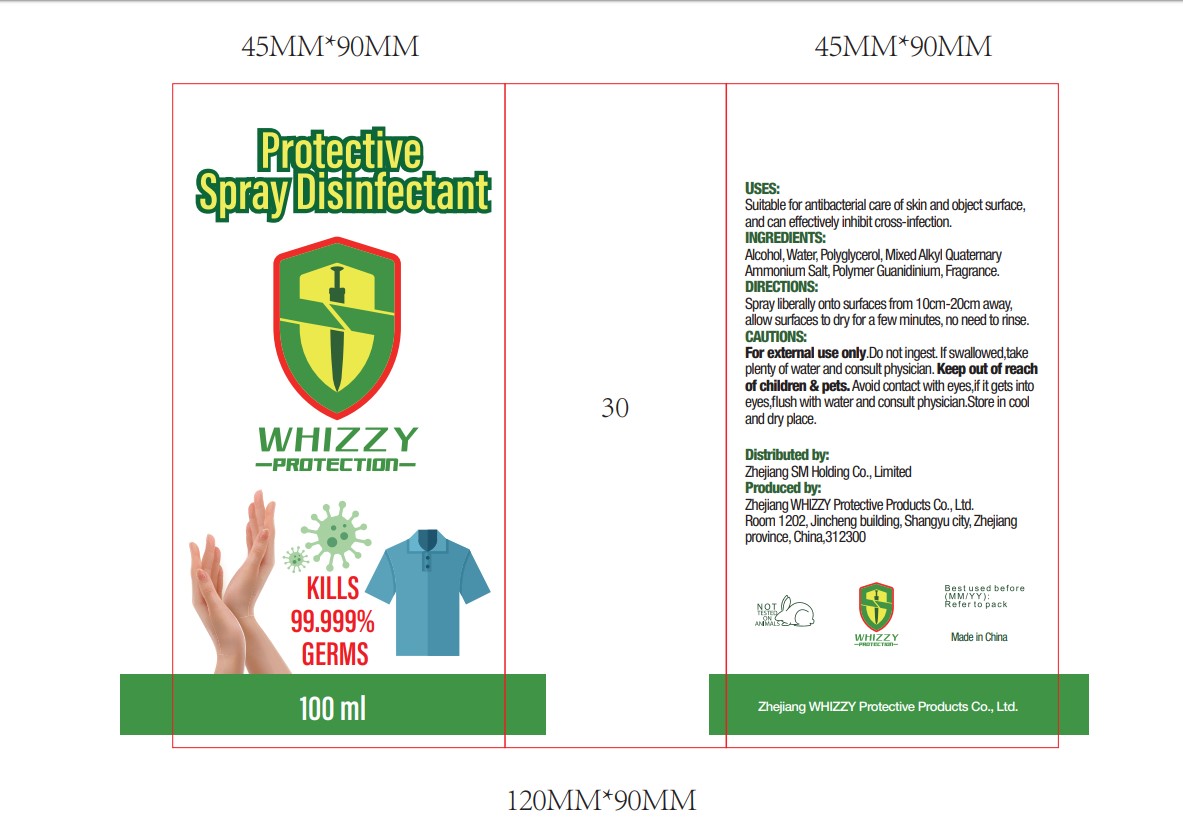 DRUG LABEL: Protective Disinfectant
NDC: 79094-003 | Form: SPRAY
Manufacturer: Zhejiang WHIZZY Protective Products Co.,Ltd
Category: otc | Type: HUMAN OTC DRUG LABEL
Date: 20200917

ACTIVE INGREDIENTS: ALCOHOL 3 mL/100 mL
INACTIVE INGREDIENTS: DIMYRISTYLDIMONIUM CHLORIDE 0.15 mL/100 mL; DILAURYLDIMONIUM CHLORIDE 0.25 mL/100 mL; WATER 93.5 mL/100 mL; DIPROPYLENE GLYCOL 0.02 mL/100 mL; POLYGLYCERIN-20 3 mL/100 mL; SPEARMINT OIL 0.005 mL/100 mL; MENTHA ARVENSIS LEAF OIL 0.015 mL/100 mL; RACEMENTHOL 0.015 mL/100 mL

PURPOSE

Kills 99.999% bacteria

USES

suitable for antibacterial care of skin and object surface,and can effectively inhibit cross-ifection

CAUTIONS

For external use only. Do not ingest.If swallowed,take plenty of water and consult physician.

Keep out of reach of children & pets.Avoid contact with eyes,if it gets into eyes,flush with

water and consult physician.Store in cool and dry place

Keep out of reach of children. If swallowed,take plenty of water and consult physician.

Directions

Spray liberally onto surfaces from 10cm-20cm away,allow surfaces to dry for a few minutes,no need to rinse.

ingredients

Alcohol,Water,Mixed Alkyl Quaternary Ammonium Salt,Polymer Guanidinium,Fragrance